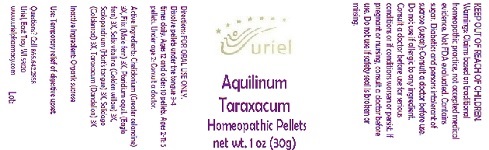 DRUG LABEL: Aquilinum Taraxicum
NDC: 48951-1070 | Form: PELLET
Manufacturer: Uriel Pharmacy Inc.
Category: homeopathic | Type: HUMAN OTC DRUG LABEL
Date: 20180531

ACTIVE INGREDIENTS: CHELIDONIUM MAJUS 3 [hp_X]/1 1; DRYOPTERIS FILIX-MAS ROOT 3 [hp_X]/1 1; PTERIDIUM AQUILINUM WHOLE 3 [hp_X]/1 1; SALIX PURPUREA BARK 3 [hp_X]/1 1; WILLOW BARK 3 [hp_X]/1 1; SALIX ALBA FLOWER 3 [hp_X]/1 1; ASPLENIUM SCOLOPENDRIUM TOP 3 [hp_X]/1 1; SOLIDAGO CANADENSIS FLOWERING TOP 3 [hp_X]/1 1; TARAXACUM PALUSTRE ROOT 3 [hp_X]/1 1
INACTIVE INGREDIENTS: SUCROSE

Aquilinum Taraxicum

INDICATIONS AND USAGE

Directions: FOR ORAL USE ONLY.

DOSAGE AND ADMINISTRATION

Dissolve pellets under the tongue 3-4 times daily. Ages 12 and older: 10 pellets. Ages 2-11: 5 pellets. Under age 2: Consult a doctor.

ACTIVE INGREDIENT

Active Ingredients: Chelidonium (Greater celandine) 3X, Filix (Male fern) 3X, Pteridium aquil. (Eagle fern) 3X, Salix vitellina (Golden willow) 3X, Scolopendrium (Hart's tongue) 3X, Solidago (Goldenrod) 3X, Taraxacum (Dandelion) 3X

Inactive Ingredient: Sucrose

PURPOSE

Use: Temporary relief of digestive upset.

KEEP OUT OF REACH OF CHILDREN.

WARNINGS

Warnings: Claims based on traditional homeopathic practice, not accepted medical evidence. Not FDA evaluated. Contains sugar. Diabetics and persons intolerant of sucrose (sugar): Consult a doctor before use. Do not use if allergic to any ingredient. Consult a doctor before use for serious conditions or if conditions worsen or persist. If pregnant or nursing, consult a doctor before use. Do not use if safety seal is broken or missing.

Questions? Call 866.642.2858
Uriel, East Troy WI 53120
www.urielpharmacy.com